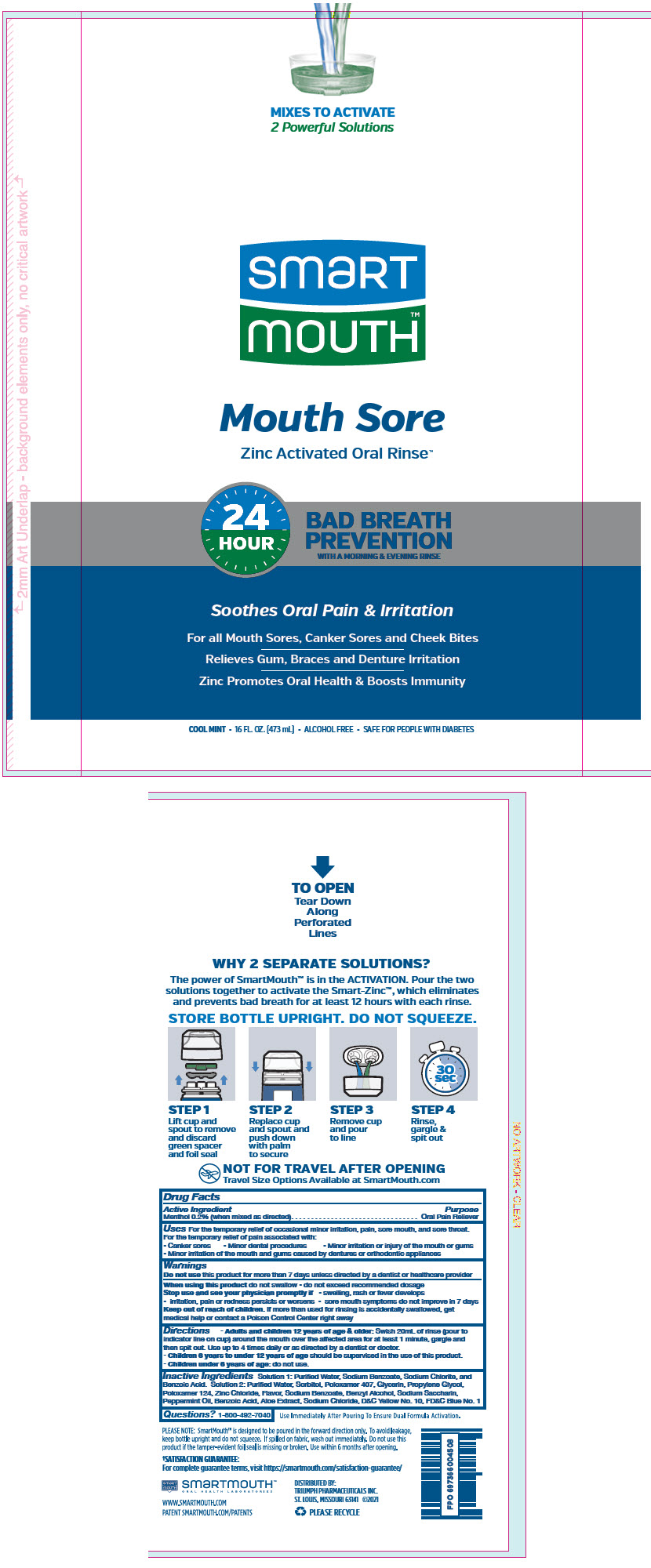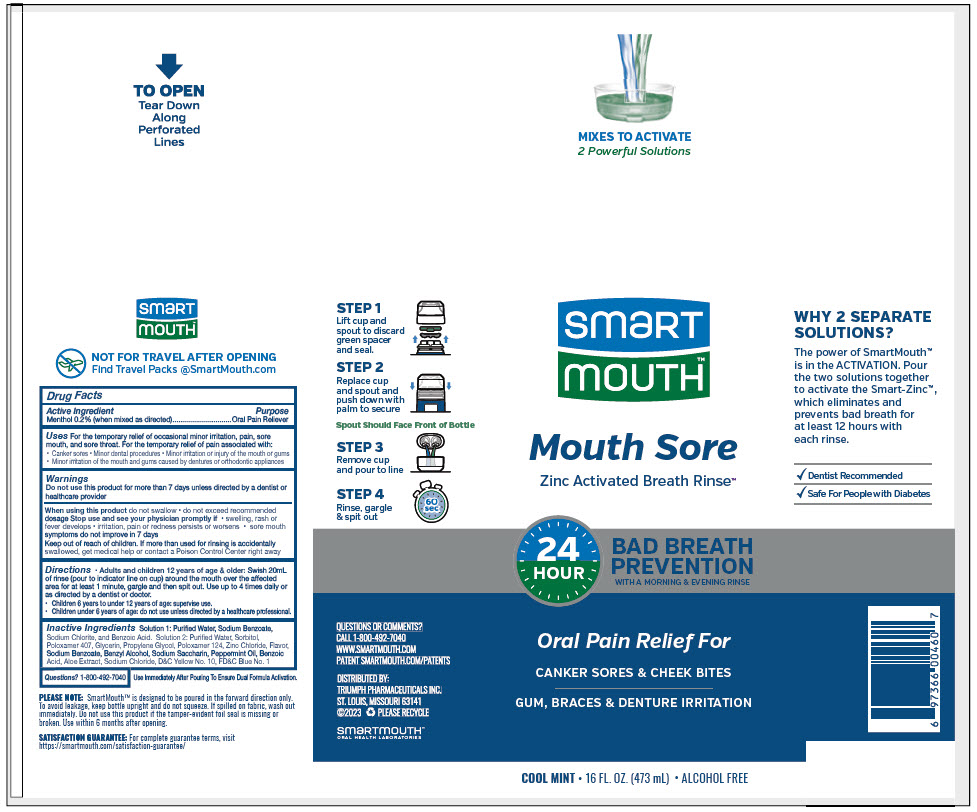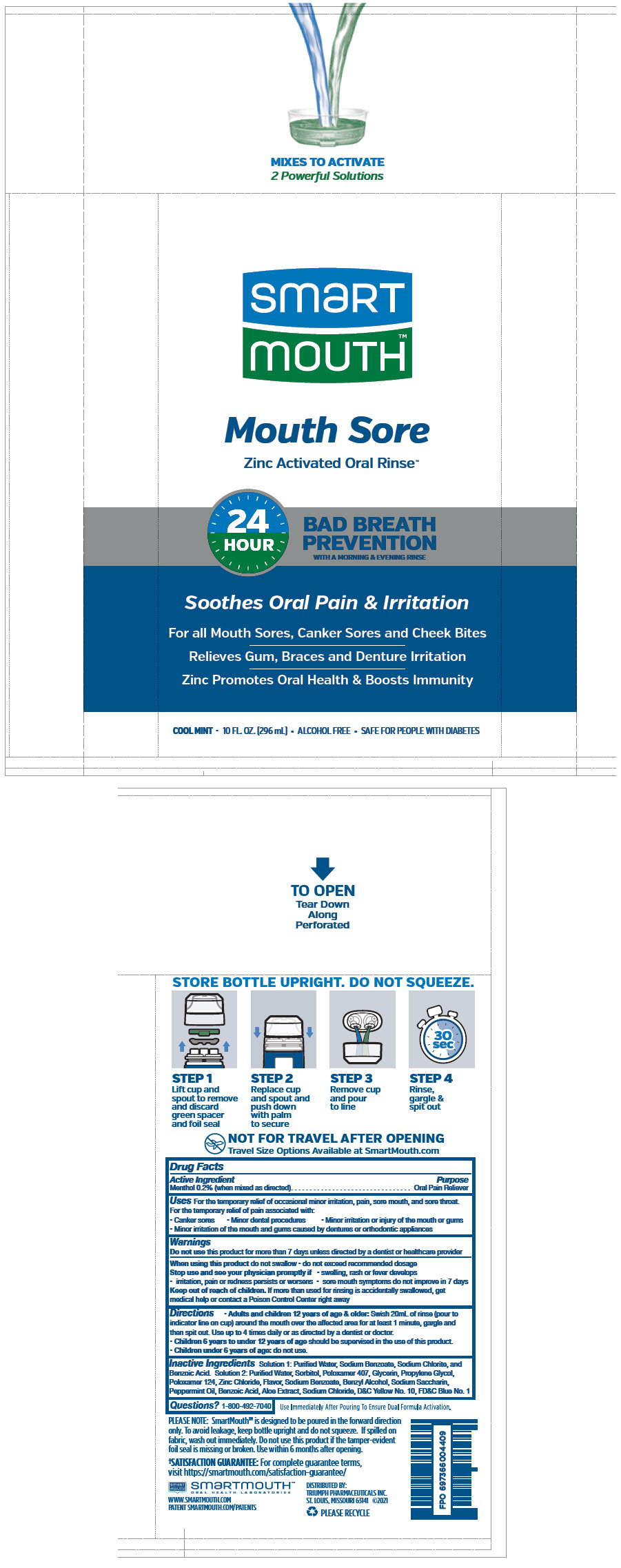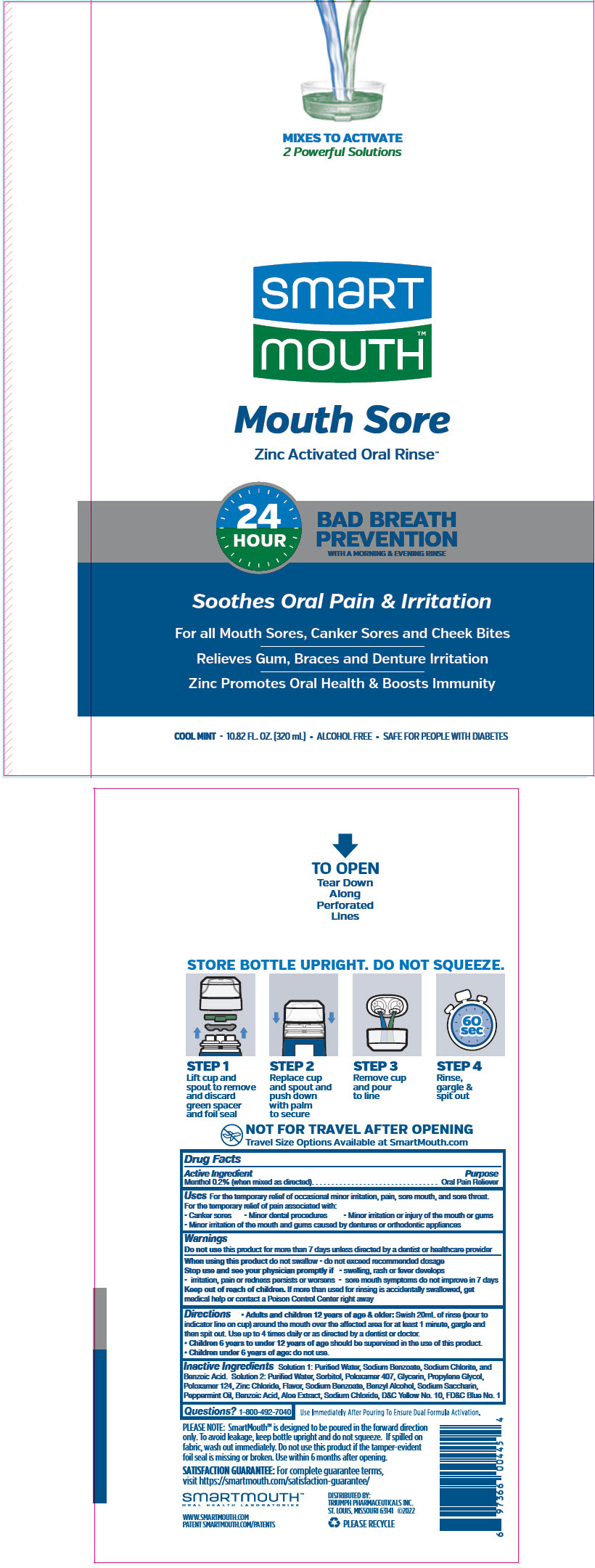 DRUG LABEL: SmartMouth 
NDC: 76357-409 | Form: KIT | Route: DENTAL
Manufacturer: Triumph Pharmaceuticals Inc.
Category: otc | Type: HUMAN OTC DRUG LABEL
Date: 20231221

ACTIVE INGREDIENTS: MENTHOL, UNSPECIFIED FORM 10 mg/20 mL
INACTIVE INGREDIENTS: Water; Sodium Benzoate; Benzoic Acid; Glycerin; Poloxamer 407; Propylene Glycol; Poloxamer 124; Zinc Chloride; Sodium; Saccharin Sodium; Sodium Chloride; Benzyl Alcohol; Sorbitol; Aloe Vera Leaf; Peppermint Oil

SmartMouth™ Mouthwash
Mouth Sore Zinc Activated Formula

Drug Facts

Active Ingredient

Menthol 0.2% (when mixed as directed)

Purpose

Oral Pain Reliever

Uses

For the temporary relief of occasional minor irritation, pain, sore mouth, and sore throat.

For the temporary relief of pain associated with:

- Canker sores
- Minor dental procedures
- Minor irritation or injury of the mouth or gums
- Minor irritation of the mouth and gums caused by dentures or orthodontic appliances

Warnings

Do not use this product for more than 7 days unless directed by a dentist or healthcare provider

When using this product do not swallow

- do not exceed recommended dosage

Stop use and see your physician promptly if

- swelling, rash or fever develops
- irritation, pain or redness persists or worsens
- sore mouth symptoms do not improve in 7 days

Keep out of reach of children. If more than used for rinsing is accidentally swallowed, get medical help or contact a Poison Control Center right away

Directions

- Adults and children 12 years of age & older: Swish 20mL of rinse (pour to indicator line on cup) around the mouth over the affected area for at least 1 minute, gargle and then spit out. Use up to 4 times daily or as directed by a dentist or doctor.
- Children 6 years to under 12 years of age should be supervised in the use of this product.
- Children under 6 years of age: do not use.

Inactive Ingredients

Solution 1: Purified Water, Sodium Benzoate, Sodium Chlorite, and Benzoic Acid. Solution 2: Purified Water, Sorbitol, Poloxamer 407, Glycerin, Propylene Glycol, Poloxamer 124, Zinc Chloride, Flavor, Sodium Benzoate, Benzyl Alcohol, Sodium Saccharin, Peppermint Oil, Benzoic Acid, Aloe Extract, Sodium Chloride, D&C Yellow No. 10, FD&C Blue No. 1

Questions?

1-800-492-7040

DISTRIBUTED BY:
TRIUMPH PHARMACEUTICALS INC.
ST. LOUIS, MISSOURI 63141

PRINCIPAL DISPLAY PANEL - 437 mL Kit Cello Pack

MIXES TO ACTIVATE
2 Powerful Solutions

smart
mouth™

Mouth Sore
Zinc Activated Oral Rinse™

24
HOUR
BAD BREATH
PREVENTION
WITH A MORNING & EVENING RINSE

Soothes Oral Pain & Irritation

For all Mouth Sores, Canker Sores and Cheek Bites

Relieves Gum, Braces and Denture Irritation

Zinc Promotes Oral Health & Boosts Immunity

COOL MINT • 16 FL. OZ. (473 mL) • ALCOHOL FREE • SAFE FOR PEOPLE WITH DIABETES

PRINCIPAL DISPLAY PANEL - 437 mL Kit Cello Pack - Breath Rinse

MIXES TO ACTIVATE
2 Powerful Solutions

smart
mouth™

Mouth Sore
Zinc Activated Breath Rinse™

24
HOUR
BAD BREATH
PREVENTION
WITH A MORNING & EVENING RINSE

Oral Pain Relief For
CANKER SORES & CHEEK BITES
GUM, BRACES & DENTURE IRRITATION

COOL MINT • 16 FL. OZ. (473 mL) • ALCOHOL FREE

PRINCIPAL DISPLAY PANEL - 296 mL Kit Cello Pack

MIXES TO ACTIVATE
2 Powerful Solutions

smart
mouth™

Mouth Sore
Zinc Activated Oral Rinse™

24
HOUR
BAD BREATH
PREVENTION
WITH A MORNING & EVENING RINSE

Soothes Oral Pain & Irritation

For all Mouth Sores, Canker Sores and Cheek Bites

Relieves Gum, Braces and Denture Irritation

Zinc Promotes Oral Health & Boosts Immunity

COOL MINT • 10 FL. OZ. (296 mL) • ALCOHOL FREE • SAFE FOR PEOPLE WITH DIABETES

PRINCIPAL DISPLAY PANEL - 320 mL Kit Cello Pack

MIXES TO ACTIVATE
2 Powerful Solutions

smart
mouth™

Mouth Sore
Zinc Activated Oral Rinse™

24
HOUR
BAD BREATH
PREVENTION
WITH A MORNING & EVENING RINSE

Soothes Oral Pain & Irritation

For all Mouth Sores, Canker Sores and Cheek Bites

Relieves Gum, Braces and Denture Irritation

Zinc Promotes Oral Health & Boosts Immunity

COOL MINT • 10.82 FL. OZ. (320 mL) • ALCOHOL FREE • SAFE FOR PEOPLE WITH DIABETES